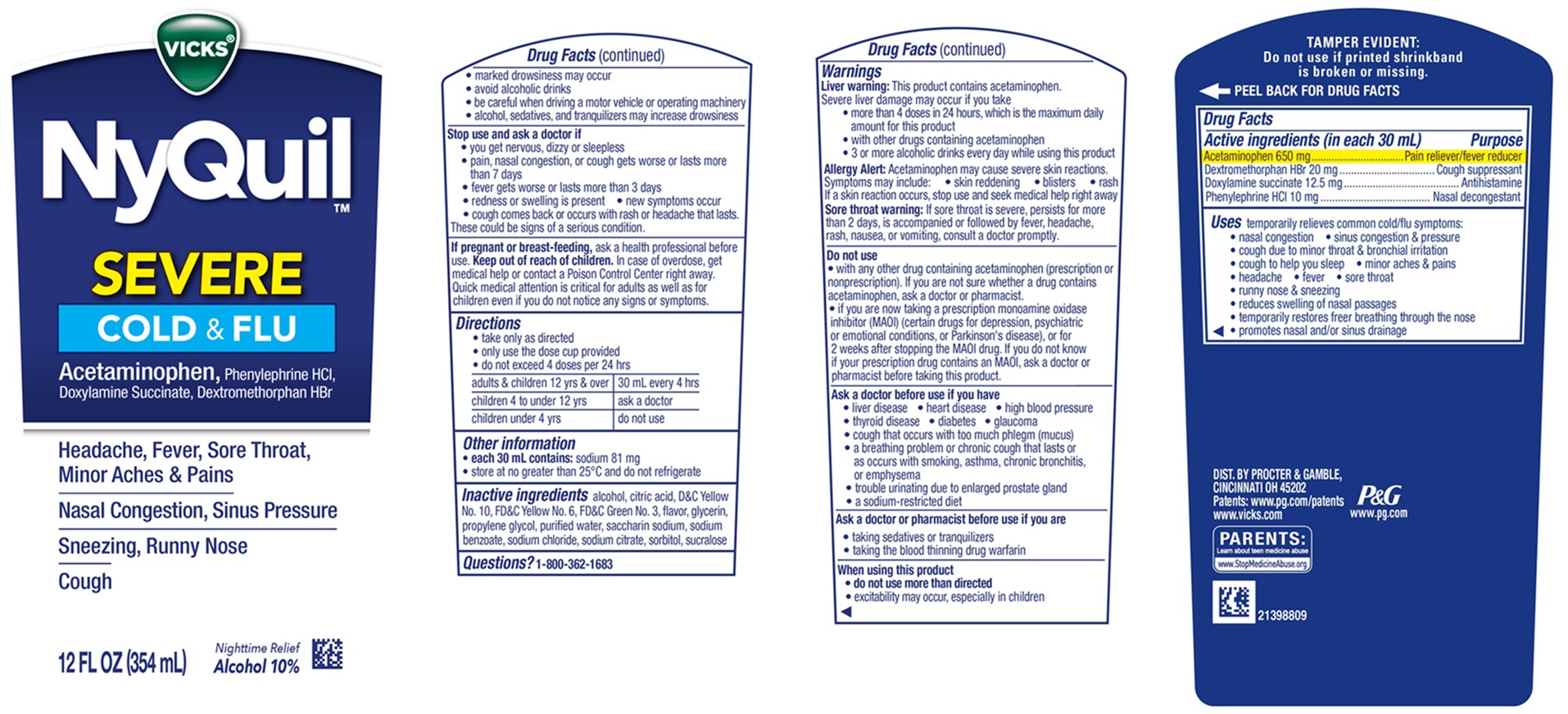 DRUG LABEL: Vicks NyQuil
NDC: 37000-815 | Form: SOLUTION
Manufacturer: The Procter & Gamble Manufacturing Company
Category: otc | Type: HUMAN OTC DRUG LABEL
Date: 20260219

ACTIVE INGREDIENTS: PHENYLEPHRINE HYDROCHLORIDE 10 mg/30 mL; DOXYLAMINE SUCCINATE 12.5 mg/30 mL; DEXTROMETHORPHAN HYDROBROMIDE 20 mg/30 mL; ACETAMINOPHEN 650 mg/30 mL
INACTIVE INGREDIENTS: ALCOHOL; CITRIC ACID MONOHYDRATE; D&C YELLOW NO. 10; FD&C YELLOW NO. 6; FD&C GREEN NO. 3; GLYCERIN; PROPYLENE GLYCOL; WATER; SACCHARIN SODIUM; SODIUM BENZOATE; SODIUM CHLORIDE; SODIUM CITRATE; SORBITOL; SUCRALOSE

Vicks®NyQuil™ Severe Cold & Flu Original Liquid

Drug Facts

Active ingredients (in each 30 mL)

Acetaminophen 650 mg
Dextromethorphan HBr 20 mg
Doxylamine succinate 12.5 mg
Phenylephrine HCl 10 mg

Purpose

Pain reliever/fever reducer
Cough suppressant
Antihistamine
Nasal decongestant

Uses

temporarily relieves common cold/flu symptoms:

- nasal congestion
- sinus congestion & pressure
- cough due to minor throat & bronchial irritation
- cough to help you sleep
- minor aches & pains
- headache
- fever
- sore throat
- runny nose & sneezing
- reduces swelling of nasal passages
- temporarily restores freer breathing through the nose
- promotes nasal and/or sinus drainage

Warnings

Liver warning:This product contains acetaminophen.
Severe liver damage may occur if you take
• more than 4 doses in 24 hours, which is the maximum daily amount for this product
• with other drugs containing acetaminophen
• 3 or more alcoholic drinks every day while using this product

Allergy Alert:Acetaminophen may cause severe skin reactions.
Symptoms may include: • skin reddening • blisters • rash
If a skin reaction occurs, stop use and seek medical help right away

Sore throat warning:If sore throat is severe, persists for more than 2 days, is accompanied or followed by fever, headache, rash, nausea, or vomiting, consult a doctor promptly.

Do not use

- with any other drug containing acetaminophen (prescription or nonprescription). If you are not sure whether a drug contains acetaminophen, ask a doctor or pharmacist.
- if you are now taking a prescription monoamine oxidase inhibitor (MAOI) (certain drugs for depression, psychiatric or emotional conditions, or Parkinson's disease), or for 2 weeks after stopping the MAOI drug. If you do not know if your prescription drug contains an MAOI, ask a doctor or pharmacist before taking this product.

Ask a doctor before use if you have

- liver disease
- heart disease
- high blood pressure
- thyroid disease
- diabetes
- glaucoma
- cough that occurs with too much phlegm (mucus)
- a breathing problem or chronic cough that lasts or as occurs with smoking, asthma, chronic bronchitis, or emphysema
- trouble urinating due to enlarged prostate gland
- a sodium-restricted diet

Ask a doctor or pharmacist before use if you are

- taking sedatives or tranquilizers
- taking the blood thinning drug warfarin

When using this product

- do not use more than directed
- excitability may occur, especially in children
- marked drowsiness may occur
- avoid alcoholic drinks
- be careful when driving a motor vehicle or operating machinery
- alcohol, sedatives, and tranquilizers may increase drowsiness

Stop use and ask a doctor if

- you get nervous, dizzy or sleepless
- pain, nasal congestion, or cough gets worse or lasts more than 7 days
- fever gets worse or lasts more than 3 days
- redness or swelling is present
- new symptoms occur
- cough comes back or occurs with rash or headache that lasts.

These could be signs of a serious condition.

If pregnant or breast-feeding,

ask a health professional before use.

Keep out of reach of children.

In case of overdose, get medical help or contact a Poison Control Center right away. Quick medical attention is critical for adults as well as for children even if you do not notice any signs or symptoms.

Directions

- take only as directed
- only use the dose cup provided
- do not exceed 4 doses per 24 hrs

adults & children 12 yrs & over | 30 mL every 4 hrs
children 4 to under 12 yrs | ask a doctor
children under 4 yrs | do not use

Other information

• each 30 mL contains: sodium 81 mg
• store at no greater than 25°C and do not refrigerate

Inactive ingredients

alcohol, citric acid, D&C Yellow No. 10, FD&C Yellow No. 6, FD&C Green No. 3, flavor, glycerin, propylene glycol, purified water, saccharin sodium, sodium benzoate, sodium chloride, sodium citrate, sorbitol, sucralose

Questions?

1-800-362-1683

TAMPER EVIDENT: Do not use if printed shrinkband is broken or missing.

DIST. BY PROCTER & GAMBLE,
CINCINNATI OH 45202

PRINCIPAL DISPLAY PANEL

VICKS®

NyQuil™
SEVERE

COLD & FLU

Acetaminophen, Phenylephrine HCl, Doxylamine Succinate, Dextromethorphan HBr

- Headache, Fever, Sore Throat, Minor Aches & Pains
- Nasal Congestion, Sinus Pressure
- Sneezing, Runny Nose
- Cough

Nighttime Relief
Alcohol 10%

12 FL OZ (354 ml)